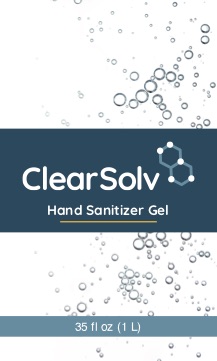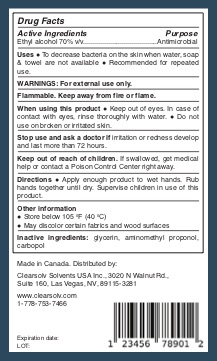 DRUG LABEL: ClearSolv Hand Sanitizing Gel
NDC: 90091-001 | Form: GEL
Manufacturer: ClearSolv Solvents USA Inc.
Category: otc | Type: HUMAN OTC DRUG LABEL
Date: 20200729

ACTIVE INGREDIENTS: ALCOHOL 700.52 mL/1000 mL
INACTIVE INGREDIENTS: GLYCERIN 6.72 mL/1000 mL; CARBOMER 940 5.09 g/1000 mL; AMINOMETHYLPROPANOL 1.64 mL/1000 mL; WATER 286.04 mL/1000 mL

Hand Sanitizer

This is a hand sanitizer manufactured according to the Temporary Policy for Preparation of Certain Alcohol-Based Hand Sanitizer Products During the Public Health Emergency (CoViD-19); Guidance for Industry. The hand sanitizer is manufactured using only the following United States Pharmacopoeia (USP) grade ingredients in the preparation of the product (percentage in final product formulation) consistent with World Health Organization (WHO) recommendations:

a. Isopropyl Alcohol (70%, v/v) in an aqueous solution denatured according to Alcohol and Tobacco Tax and Trade Bureau regulations in 27 CFR part 20.

b. Glycerol (1.0% v/v).

c. Carbopol 940 (0.40% v/v).

d. Aminomethyl proponol (0.1% v/v)

d. Sterile distilled water or boiled cold water.

. The firm does not add other active or inactive ingredients. Different or additional ingredients may impact the quality and potency of the product.

ACTIVE INGREDIENT

Alcohol 70% v/v. Purpose: Antiseptic

PURPOSE

Antiseptic, Hand Sanitizer

INDICATIONS AND USAGE

Hand Sanitizer to help reduce bacteria that potentially can cause disease. For use when soap and water are not available.

WARNINGS

For external use only. Flammable. Keep away from heat or flame.

DO NOT USE

in children less than 2 months of age

on open skin wounds

When using this product keep out of eyes, ears, and mouth. In case of contact with eyes, rinse eyes thoroughly with water.

Stop use and ask a doctor if irritation or rash occurs. These may be signs of a serious condition.
Keep out of reach of children. If swallowed, get medical help or contact a Poison Control Center right away.

Stop use and ask a doctor if irritation or rash occurs. These may be signs of a serious condition.

Keep out of reach of children. If swallowed, get medical help or contact a Poison Control Center right away.

DOSAGE AND ADMINISTRATION

Place enough product on hands to cover all surfaces. Rub hands together until dry.

Supervise children under 6 years of age when using this product to avoid swallowing.

STORAGE AND HANDLING

Store between 15-30C (59-86F).

Avoid freezing and excessive heat above 40C (104F)

INACTIVE INGREDIENT

glycerin, carbopol 940, aminomethyl proponol, purified water USP

PACKAGE LABEL

000 ml NDC: 90091-001-00